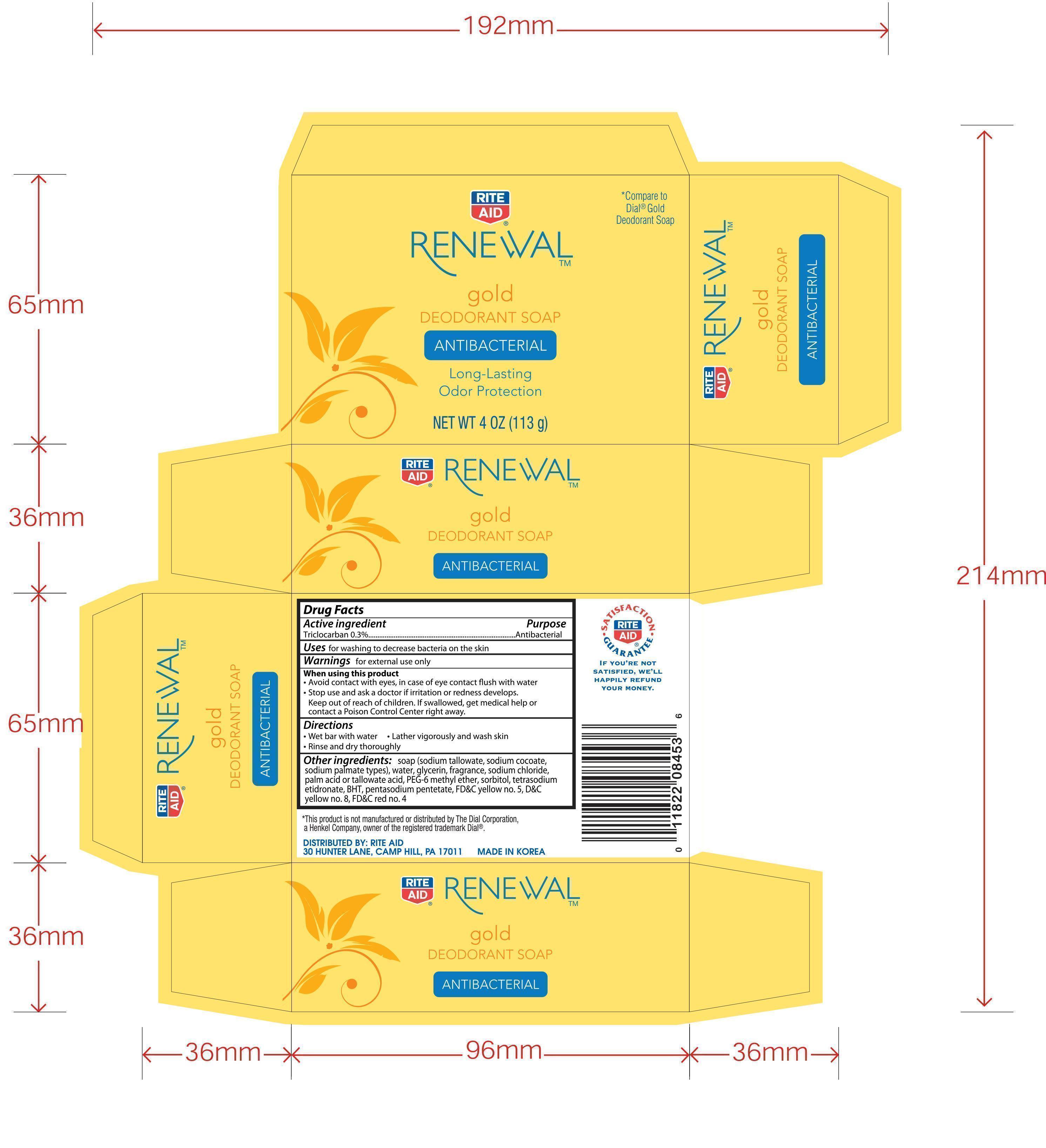 DRUG LABEL: Rite Aid Renewal Gold Deodorant
NDC: 11822-8453 | Form: SOAP
Manufacturer: Rite Aid Corporation
Category: otc | Type: HUMAN OTC DRUG LABEL
Date: 20140730

ACTIVE INGREDIENTS: TRICLOCARBAN 0.3 g/1 g
INACTIVE INGREDIENTS: COCONUT ACID; GLYCERIN; PEG-6 METHYL ETHER; PENTASODIUM PENTETATE; SODIUM COCOATE; SODIUM PALMATE; SORBITOL; ETIDRONATE TETRASODIUM; WATER; SODIUM CHLORIDE; PALM ACID; FD&C YELLOW NO. 5; D&C YELLOW NO. 8; FD&C RED NO. 4; TALLOW ACID, BEEF

Active Ingredients

Triclocarban 0.3%-------------------------------------------------Antibacterial

Uses

for washing to decrease bacteria on the skin

Warnings for external use only.

When using this product

- Avoid contact with eyes. In case of ee contact, flush with water

- Stop use and ask a doctor if irritation or redness develops

KEEP OUT OF REACH OF CHILDREN

- Keep out ot reach of children. If swallowed, get medical help or contact a Poison Control Center right away.

Directions.

- Wet bar with water
- Lather vigorously and wash skin
- Rinse and dry thoroughly

INACTIVE INGREDIENT

Other ingredients: soap (sodium tallowate, sodium cocoate, sodium palmate types), water, glycerin, fragrance, sodium chloride, palm acid or tallowate acid, PEG-6 methyl ether, sorbitol, tetrasodium etidronate, BHT, pentasodium pentetate, FD&C yellow no. 5, D&C yellow no. 8, FD&C red no.4

DOSAGE AND ADMINISTRATION

Distributed by: Rite Aid

30 Hunter Lane, Camp Hill, PA17011

Made in Korea